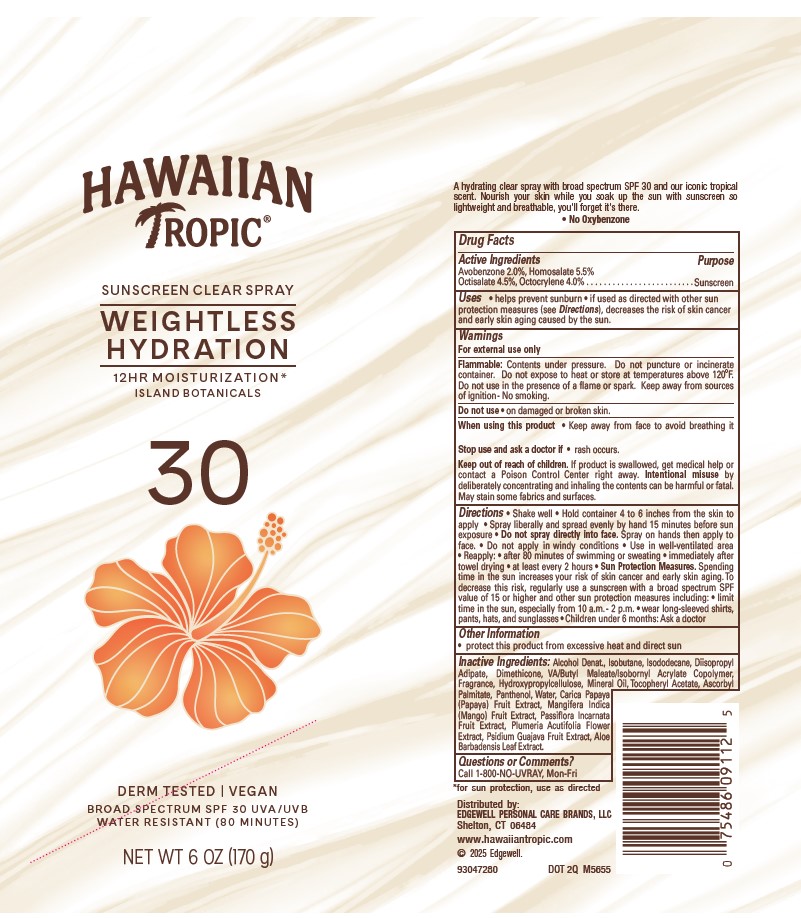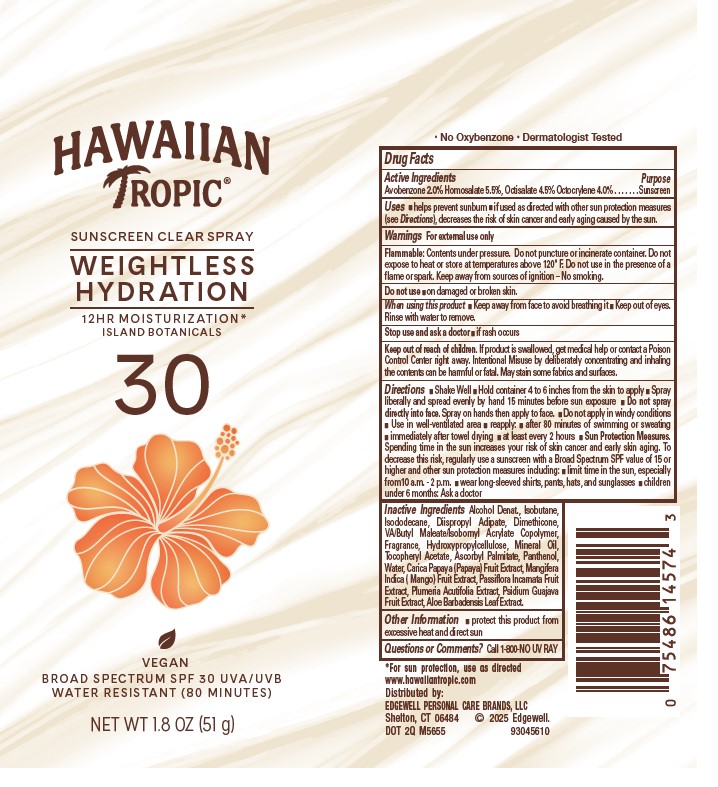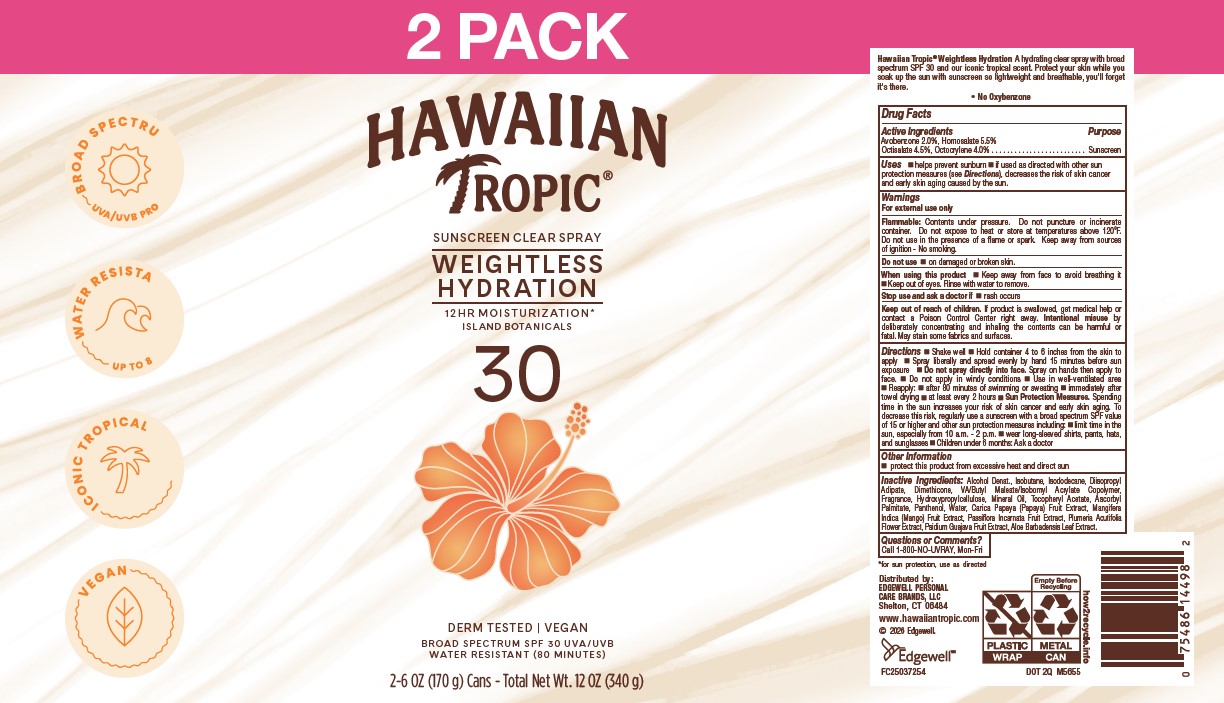 DRUG LABEL: HAWAIIAN TROPIC
NDC: 63354-894 | Form: AEROSOL, SPRAY
Manufacturer: Edgewell Personal Care Brands LLC
Category: otc | Type: HUMAN OTC DRUG LABEL
Date: 20260106

ACTIVE INGREDIENTS: AVOBENZONE 2 g/100 g; HOMOSALATE 5.5 g/100 g; OCTOCRYLENE 4 g/100 g; OCTISALATE 4.5 g/100 g
INACTIVE INGREDIENTS: PANTHENOL; MINERAL OIL; ALOE VERA LEAF; MANGO; GUAVA; ALPHA-TOCOPHEROL ACETATE; ASCORBYL PALMITATE; PAPAYA; ALCOHOL; DIMETHICONE; PLUMERIA RUBRA FLOWER; PASSIFLORA INCARNATA FRUIT; WATER; DIISOPROPYL ADIPATE; ISODODECANE; ISOBUTANE; HYDROXYPROPYL CELLULOSE, UNSPECIFIED

Active Ingredient

Avobenzone 2.0%, Homosalate 5.5%, Octisalate 4.5%, Octocrylene 4.0%

Purpose

Sunscreen

Uses

• helps prevent sunburn • if used as directed with other sun protection measures (see Directions), decreases the risk of skin cancer and early skin aging caused by the sun.

Warnings

For external use only

Flammable: Contents under pressure. Do not puncture or incinerate container. Do not expose to heat or store at temperatures above 120oF. Do not use in the presence of a flame or spark. Keep away from sources of ignition - No smoking.

May stain some fabrics and surfaces.

Do not use

on damaged or broken skin.

When using this product

• Keep away from face to avoid breathing it • Keep out of eyes. Rinse with water to remove.

Stop use and ask a doctor

if rash occurs

Keep out of reach of children.

If product is swallowed, get medical help or contact a Poison Control Center right away. Intentional misuse by deliberately concentrating and inhaling the contents can be harmful or fatal. May stain some fabrics and surfaces.

Directions

• Shake well • Hold container 4 to 6 inches from the skin to apply • Spray liberally and spread evenly by hand 15 minutes before sun exposure • Do not spray directly into face. Spray on hands then apply to face. • Do not apply in windy conditions • Use in well-ventilated area • Reapply: • after 80 minutes of swimming or sweating • immediately after towel drying • at least every 2 hours • Sun Protection Measures. Spending time in the sun increases your risk of skin cancer and early skin aging. To decrease this risk, regularly use a sunscreen with a broad spectrum SPF value of 15 or higher and other sun protection measures including: • limit time in the sun, especially from 10 a.m. - 2 p.m. • wear long-sleeved shirts, pants, hats, and sunglasses • Children under 6 months: Ask a doctor

Inactive Ingredients:

Alcohol Denat., Isobutane, Isododecane, Diisopropyl Adipate, Dimethicone, VA/Butyl Maleate/Isobornyl Acrylate Copolymer, Fragrance, Hydroxypropylcellulose, Mineral Oil, Tocopheryl Acetate, Ascorbyl Palmitate, Panthenol, Water, Carica Papaya (Papaya) Fruit Extract, Mangifera Indica (Mango) Fruit Extract, Passiflora Incarnata Fruit Extract, Plumeria Acutifolia Flower Extract, Psidium Guajava Fruit Extract, Aloe Barbadensis Leaf Extract.

Other Information

• protect this product from excessive heat and direct sun

Questions or Comments?

Call 1-800-NO-UVRAY, Mon-Fri

PRINCIPAL DISPLY PANEL

HAWAIIAN
TROPIC
SUNSCREEN CLEAR SPRAY
WEIGHTLESS
HYDRATION
12HR MOISTURIZATION*
ISLAND BOTANICALS
30
DERM TESTED | VEGAN
BROAD SPECTRUM SPF 30 UVA/UVB
WATER RESISTANT (80 MINUTES)
NET WT 6 OZ (170 g)

HAWAIIAN

TROPIC
SUNSCREEN CLEAR SPRAY
WEIGHTLESS
HYDRATION
12HR MOISTURIZATION*
ISLAND BOTANICALS
30
VEGAN
BROAD SPECTRUM SPF 30 UVA/UVB
WATER RESISTANT (80 MINUTES)
NET WT 1.8 OZ (51 g)

2PACK

HAWAIIAN
TROPIC
SUNSCREEN CLEAR SPRAY
WEIGHTLESS
HYDRATION
12HR MOISTURIZATION*
ISLAND BOTANICALS
30
DERM TESTED | VEGAN
BROAD SPECTRUM SPF 30 UVA/UVB
WATER RESISTANT (80 MINUTES)
2- 6 OZ (170 g) Cans- Total NET Wt. 12 OZ (340 g)